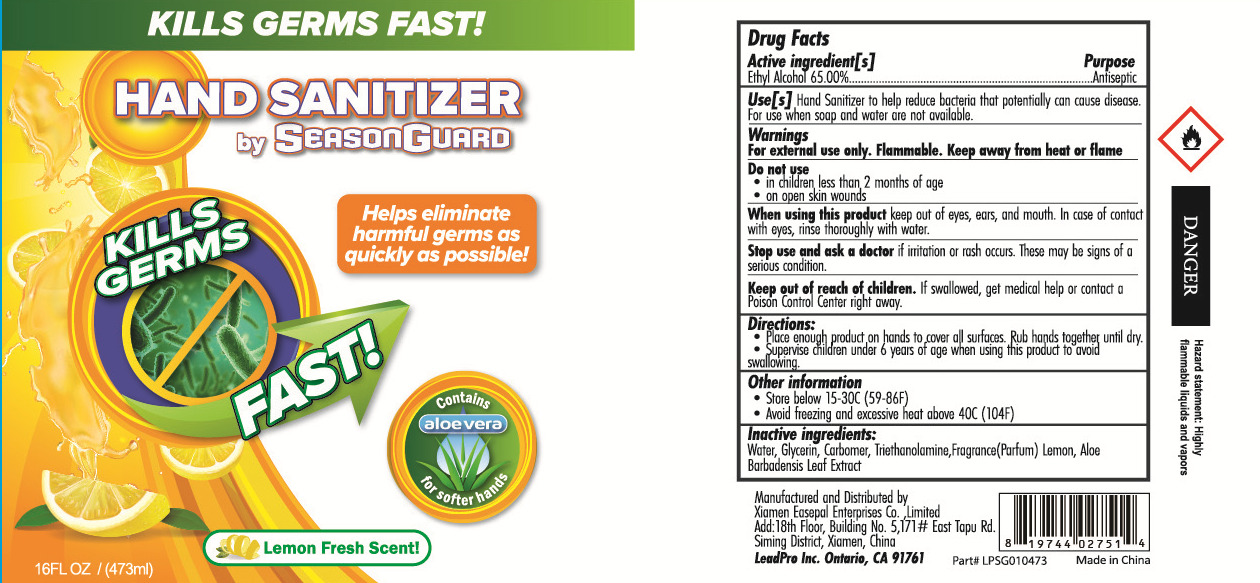 DRUG LABEL: Aloe Vera Hand Sanitizer
NDC: 67984-004 | Form: GEL
Manufacturer: XIAMEN EASEPAL ENTERPRISES LIMITED
Category: otc | Type: HUMAN OTC DRUG LABEL
Date: 20200430

ACTIVE INGREDIENTS: ALCOHOL 307.45 mL/473 mL
INACTIVE INGREDIENTS: FD&C YELLOW NO. 5; D&C RED NO. 33; FD&C RED NO. 4; TROLAMINE; GLYCERIN; FD&C BLUE NO. 1; FRAGRANCE LAVENDER & CHIA F-153480; WATER; CARBOMER HOMOPOLYMER, UNSPECIFIED TYPE

DOSAGE AND ADMINISTRATION

1.Store below 15 30C (59 86F).
2.Avoid feezing and exessve heat above 40C (104F).

INACTIVE INGREDIENT

WATER

GLYCERIN

CARBOMER

TRIETHANOLAMINE

FRAGRANCE

1) FD&C RED NO.4 (CI14700)
2) FD&C YELLOW NO.5 (CI19140)
3) FD&C BLUE NO.1 (CI42090)
4) D&C RED NO.33 (CI17200)

INDICATIONS AND USAGE

1.Place enough poducton bonds to cover a sufare. Rub honds together unil dry.
2.Supervise Cildren under 6 years of age when using this produdt to avoid.

ACTIVE INGREDIENT

ALCOHOL

keep out of reach of children

PURPOSE

Disinfection
Sterilization
No Rinseing

WARNINGS

For external use only. Flammable. Keep away from heat or flame Do not use in cildren less than2 months of age .on open skin woundsWhen using this product keep out of eye,ears, and mouth. In case of contat with eyes, rinse thoroughly with water.
Stop use and ask a doctor if itationo or rash ocus. These moy be signs of a senious condition.Keep gut of reach of children. If sollowed, get medical help or contorl Poison Control Center right away.